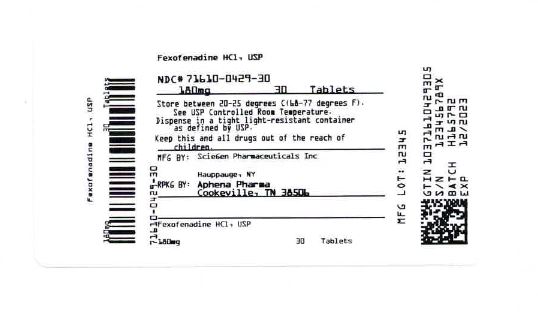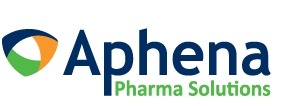 DRUG LABEL: Fexofenadine Hydrochloride
NDC: 71610-429 | Form: TABLET
Manufacturer: Aphena Pharma Solutions - Tennessee, LLC
Category: otc | Type: HUMAN OTC DRUG LABEL
Date: 20200604

ACTIVE INGREDIENTS: FEXOFENADINE HYDROCHLORIDE 180 mg/1 1
INACTIVE INGREDIENTS: SILICON DIOXIDE; CROSCARMELLOSE SODIUM; HYPROMELLOSES; FERRIC OXIDE RED; FERRIC OXIDE YELLOW; ANHYDROUS LACTOSE; STARCH, CORN; POLYETHYLENE GLYCOL, UNSPECIFIED; LACTOSE MONOHYDRATE; STEARIC ACID; TITANIUM DIOXIDE

Major Pharmaceuticals

Active ingredient (in each film-coated tablet)

Fexofenadine HCL 180 mg

Purpose

Antihistamine

Uses

temporarily relieves these symptoms due to hay fever or other upper respiratory allergies:

- runny nose
- itchy, watery eyes
- sneezing
- itching of the nose or throat

Warnings

Do not use

if you have ever had an allergic reaction to this product or any of its ingredients.

Ask a doctor before use if you have

kidney disease. Your doctor should determine if you need a different dose.

When using this product

- do not take more than directed
- do not take at the same time as aluminum or magnesium antacids
- do not take with fruit juices (see Directions)

Stop use and ask a doctor if

an allergic reaction to this product occurs. Seek medical help right away.

If pregnant or breast-feeding,

ask a health professional before use.

Keep out of reach of children.

In case of overdose, get medical help or contact a Poison Control Center right away (1-800-222-1222).

Directions

adults and children 12 years of age and over | take one 180 mg tablet with water once a day; do not take more than 1 tablet in 24 hours
children under 12 years of age | do not use
adults 65 years of age and older | ask a doctor
consumers with kidney disease | ask a doctor

Other information

- each tablet contain: sodium 8 mg
- store between 20 to 25°C (68 to 77°F)
- protect from excessive moisture
- this product meets the requirements of USP Dissolution Test 2

Inactive ingredients

anhydrous lactose, colloidal silicon dioxide, corn starch, croscarmellose sodium, hypromellose, lactose monohydrate, polyethylene glycol, pregelatinized starch (maize), red iron oxide, stearic acid, titanium dioxide, and yellow iron oxide

Questions or comments?

Call: 1-800-616-2471

Repackaging Information

Please reference the How Supplied section listed above for a description of individual tablets. This drug product has been received by Aphena Pharma - TN in a manufacturer or distributor packaged configuration and repackaged in full compliance with all applicable cGMP regulations. The package configurations available from Aphena are listed below:

Count | 180 mg
30 | 71610-429-30

Store between 20°-25°C (68°-77°F). See USP Controlled Room Temperature. Dispense in a tight light-resistant container as defined by USP. Keep this and all drugs out of the reach of children.

Repackaged by:
Cookeville, TN 38506
20200527JH

PRINCIPAL DISPLAY PANEL - 180 mg

NDC 71610-429 - Fexofenadine HCl, USP 180 mg Tablets